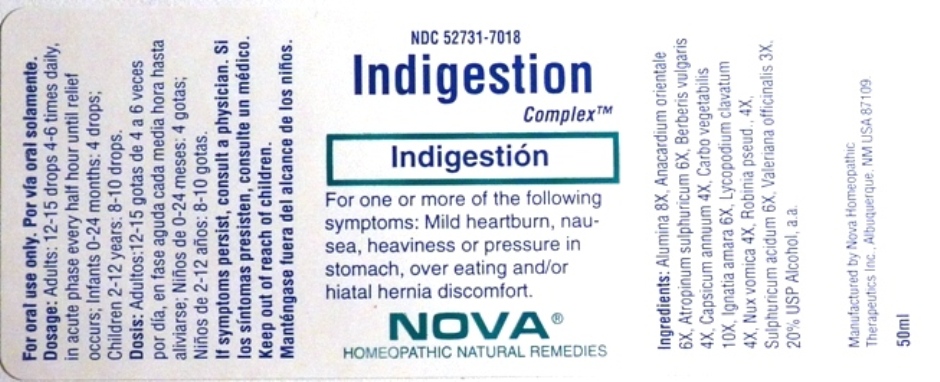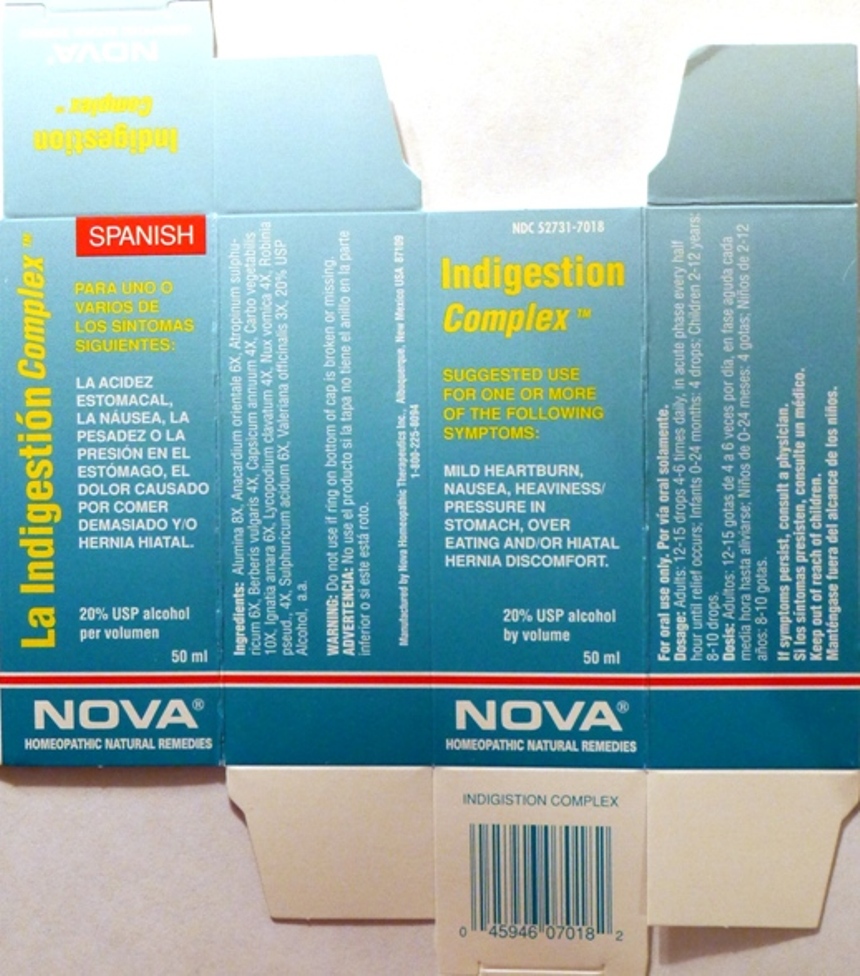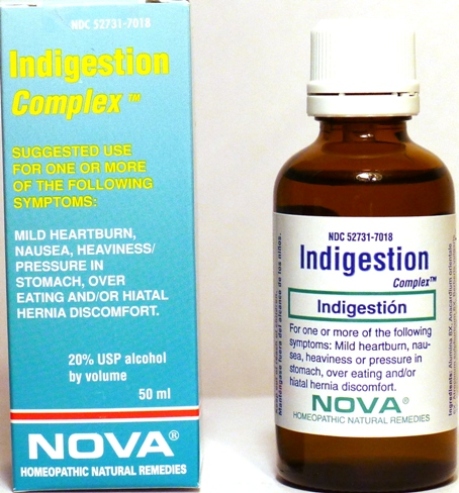 DRUG LABEL: Indigestion Complex
NDC: 52731-7018 | Form: LIQUID
Manufacturer: Nova Homeopathic Therapeutics, Inc.
Category: homeopathic | Type: HUMAN OTC DRUG LABEL
Date: 20110601

ACTIVE INGREDIENTS: ALUMINUM OXIDE 8 [hp_X]/1 mL; SEMECARPUS ANACARDIUM JUICE 6 [hp_X]/1 mL; ATROPINE SULFATE 6 [hp_X]/1 mL; BERBERIS VULGARIS ROOT BARK 4 [hp_X]/1 mL; CAPSICUM 4 [hp_X]/1 mL; ACTIVATED CHARCOAL 10 [hp_X]/1 mL; STRYCHNOS IGNATII SEED 6 [hp_X]/1 mL; LYCOPODIUM CLAVATUM SPORE 4 [hp_X]/1 mL; STRYCHNOS NUX-VOMICA SEED 4 [hp_X]/1 mL; ROBINIA PSEUDOACACIA BARK 4 [hp_X]/1 mL; SULFURIC ACID 6 [hp_X]/1 mL; VALERIAN 3 [hp_X]/1 mL
INACTIVE INGREDIENTS: ALCOHOL

Indigestion Complex

Purpose:

Suggested use for one or more of the following symptoms:

Mild Heartburn, Nausea, Heaviness/Pressure in stomach, over eating and/or hiatal hernia discomfort.

Usage and Dosage:

For oral use only.

DOSAGE AND ADMINISTRATION

Adults:
In Acute Phase:
12-15 drops, every half hour until relief occurs
When Relief Occurs:
12-15 drops, 4-6 times per day
Children 2-12 years:
8-10 drops, 4-6 times per day
Infants 0-24 months:
4 drops, 4-6 times per day

Warnings:

Keep out of reach of children.

WARNINGS

If symptoms persist, consult a physician.
Do not use if ring on bottom of cap is broken or missing.

Active Ingredients:

Alumina 8X, Anacardium orientale 6X, Atropinum sulphuricum 6X, Berberis vulgaris 4X, Capsicum annuum 4X, Carbo vegetabilis 10X, Ignatia amara 6X, Lycopodium clavatum 4X, Nux vomica 4X, Robinia pseud., 4X, Sulphuricum acidum 6X, Valeriana officinalis 3X

Inactive Ingredients:

Alcohol, 20% USP

QUESTIONS

Manufactured by Nova Homeopathic Therapeutics Inc., Albuquerque, New Mexico USA 87109
1-800-225-8094

PACKAGE LABEL

Indigestion Complex Product

Indigestion Complex Bottle Label

Indigestion Complex Box